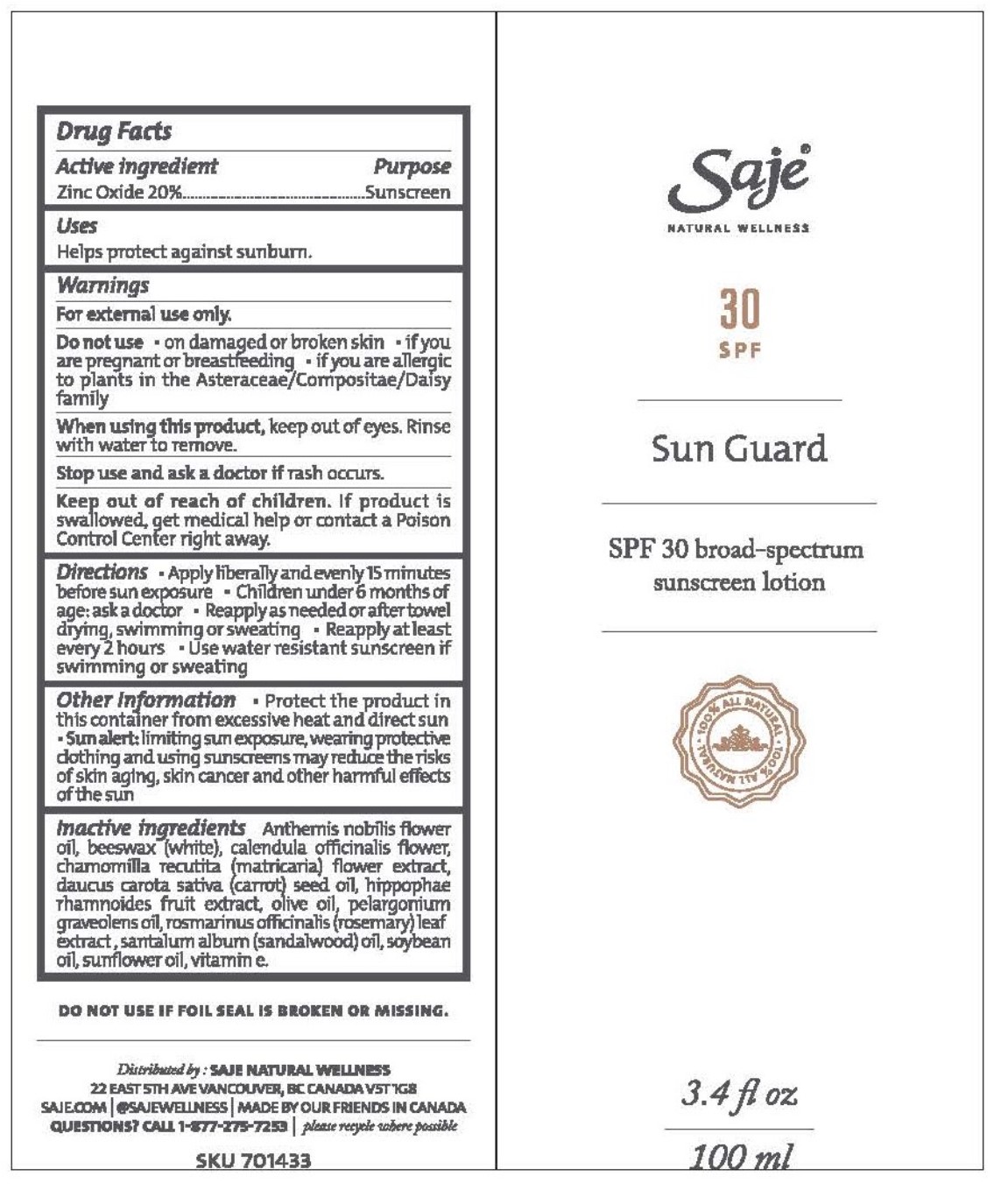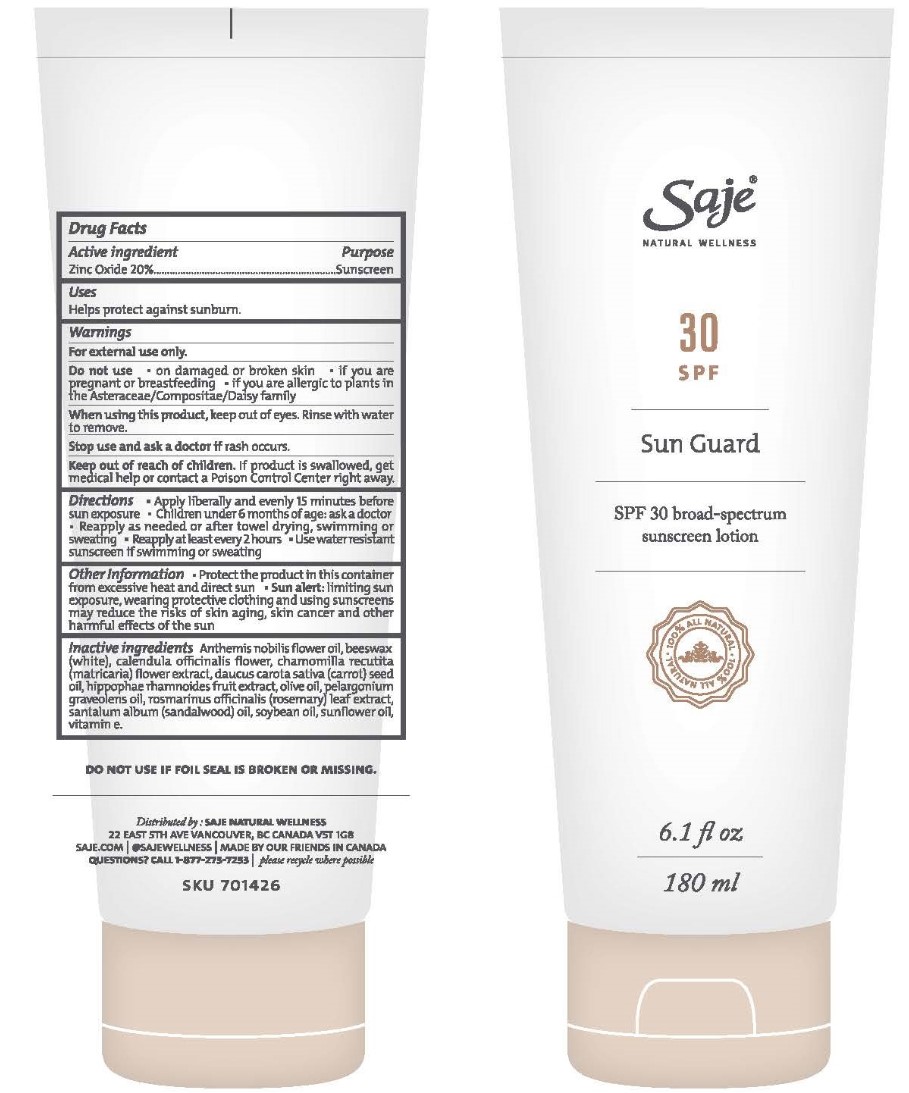 DRUG LABEL: Sun Guard
NDC: 70983-024 | Form: LOTION
Manufacturer: Saje Natural Business Inc
Category: otc | Type: HUMAN OTC DRUG LABEL
Date: 20260113

ACTIVE INGREDIENTS: ZINC OXIDE 20 mg/1 mL
INACTIVE INGREDIENTS: HIPPOPHAE RHAMNOIDES FRUIT; OLIVE OIL; PELARGONIUM GRAVEOLENS FLOWERING TOP; ROSEMARY; SOYBEAN OIL; SUNFLOWER OIL; CHAMAEMELUM NOBILE FLOWER OIL; WHITE WAX; CALENDULA OFFICINALIS FLOWER; CARROT SEED OIL; SANDALWOOD OIL; ALPHA-TOCOPHEROL; CHAMOMILE

Sun Guard

ACTIVE INGREDIENT

Zinc Oxide 20%

PURPOSE

Sunscreen

INDICATIONS AND USAGE

Helps protect against sunburn.

WARNINGS

For external use only.

Do not use if foil seal is broken or missing

Do not use • on damaged or broken skin • if you are pregnant or breastfeeding • if you are allergic to plants in the Asteraceae/Compositae/Daisy family

When using this product, keep out of eyes. Rinse with water to remove

Stop use and ask a doctor if rash occurs.

Keep out of reach of children. If product is swallowed, get medical help or contact a Poison Control Center right away.

DOSAGE AND ADMINISTRATION

Directions • Apply liberally and evenly 15 minutes before sun exposure • Children under 6 months of age: ask a doctor • Reapply as needed or after towel drying, swimming or sweating. • Reapply at least every 2 hours • Use water resistant sunscreen if swimming or sweating.

OTHER SAFETY INFORMATION

• Protect the product in this container from excessive heat and direct sun. • Sun alert: Limiting sun exposure, wearing protective clothing and using sunscreens may reduce the risks of skin aging, skin cancer and other harmful effects of the sun.
Questions? 1-877-275-7253

distributed by : saje natural wellness 22 east 5th ave vancouver, bc canada v5t 1g8 saje.com 1-877-ask-saje @sajewellness made by our friends in canada

INACTIVE INGREDIENT

Anthemis nobilis flower oil, beeswax (white), calendula officinalis flower, chamomilla recutita (matricaria) flower extract, daucus carota sativa (carrot) seed oil, hippophae rhamnoides fruit extract, olive oil, pelargonium graveolens oil, rosmarinus officinalis (rosemary) leaf extract , santalum album (sandalwood) oil, soybean oil, sunflower oil, vitamin e.

DESCRIPTION

SPF 30 Broad-Spectrum Sunscreen Lotion
3.4 fl. oz. | 100ml
6.1 fl. oz. | 180 ml